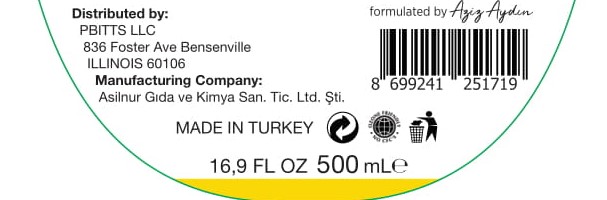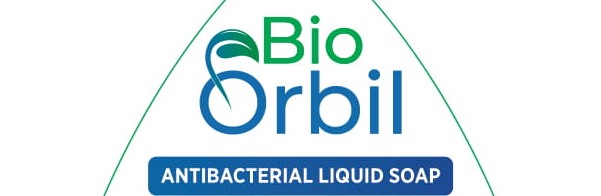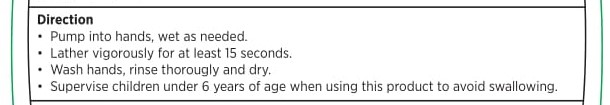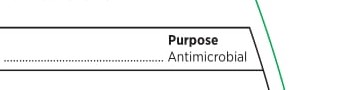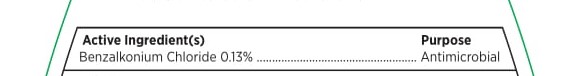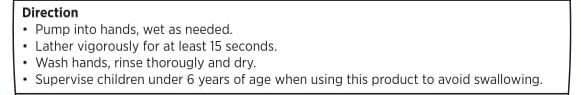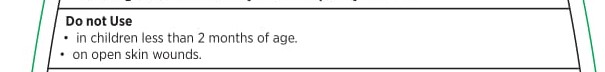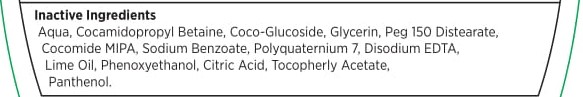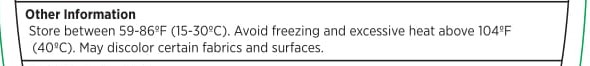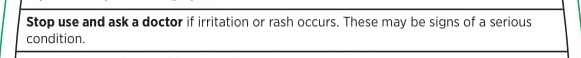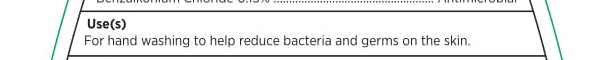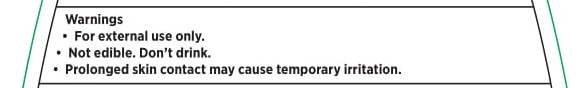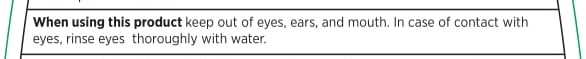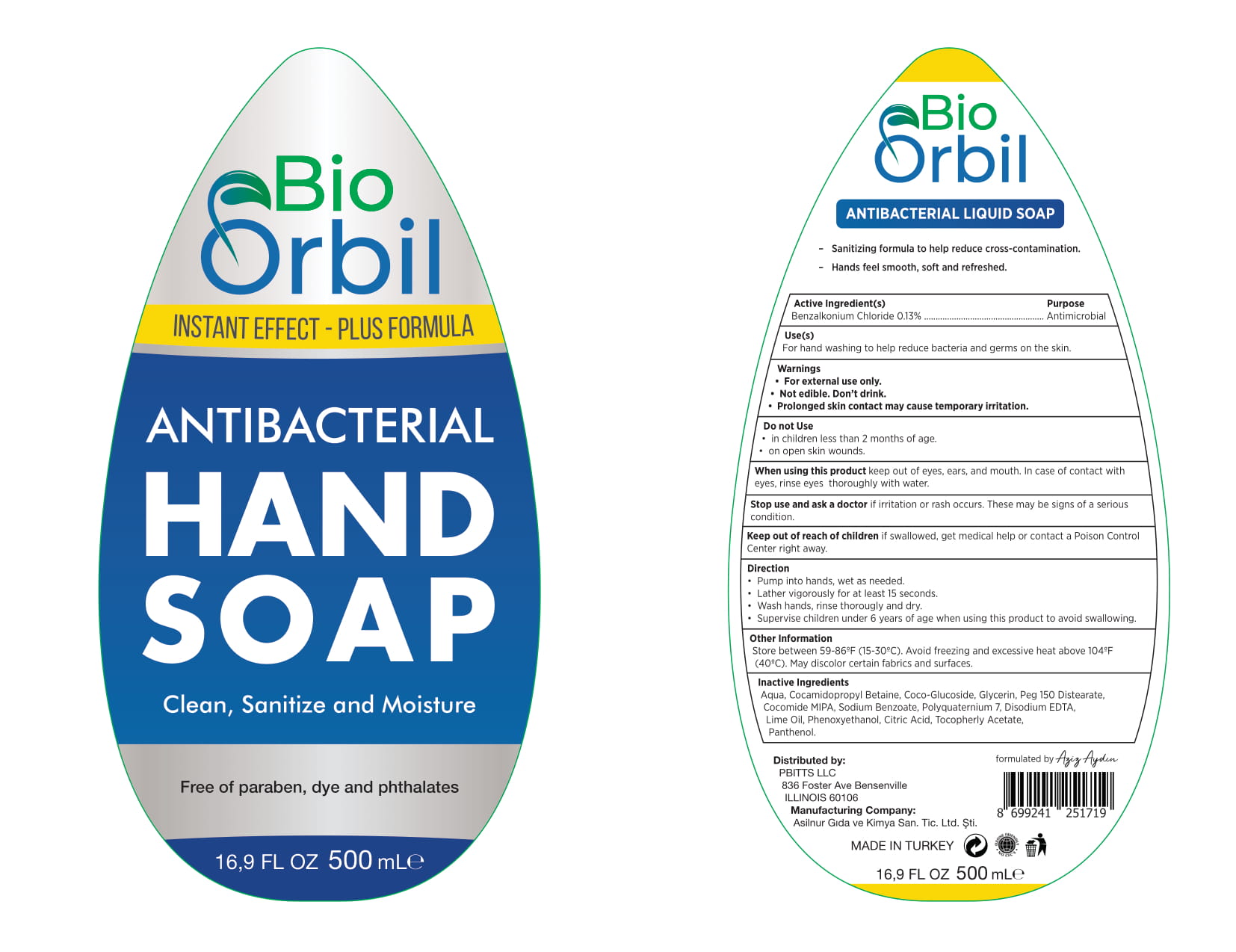 DRUG LABEL: BioOrbil ANTIBACTERIAL HANDSOAP
NDC: 81396-101 | Form: LIQUID
Manufacturer: ASILNUR GIDA VE KIMYA SANAYI TICARET LIMITED SIRKETI
Category: otc | Type: HUMAN OTC DRUG LABEL
Date: 20210111

ACTIVE INGREDIENTS: BENZALKONIUM CHLORIDE 1.3 mg/1 mL
INACTIVE INGREDIENTS: SODIUM CHLORIDE; LIME OIL; COCAMIDOPROPYL BETAINE; COCO MONOISOPROPANOLAMIDE; GLYCERIN; EDETIC ACID; COCO GLUCOSIDE; PHENOXYETHANOL; .ALPHA.-TOCOPHEROL ACETATE; WATER; PEG-150 DISTEARATE; POLYQUATERNIUM-7 (70/30 ACRYLAMIDE/DADMAC; 1600000 MW); SODIUM BENZOATE; CITRIC ACID MONOHYDRATE

Identity

BioOrbil ANTIBACTERIAL HAND SOAP

Active lngredient(s)

Benzalkonium Chloride 0.13%

Purpose

Antimicrobial

Use(s)

For hand washing to help reduce bacteria and germs on the skin.

Warnings

- For external use only.
- Not edible. Don' t drink.
- Prolonged skin contact may cause temporary irritation.

DO NOT USE

- in children less than 2 months of age.
- on open skin wounds.

When using this product keep out of eyes, ears, and mouth. In case of contact with eyes, rinse eyes thoroughly with water.

Stop use and ask a doctor if irritation or rash occurs. These may be signs of a serious condition.

Direction

- Pump into hands,wet as needed.
- Lather vigorously for at least 15 seconds.
- Wash hands, rinse thoroughly and dry.
- Supervise children under 6 years of age when using this product to avoid swallowing.

Other Information

Store between 59-86°F (15-30°C). Avoid freezing and excessive heat above 104°F(40°C). May discolor certain fabrics and surfaces.

Inactive Ingredients

Aqua, Cocamidopropyl Betaine, Coco-Glucoside, Glycerin, Peg 150 Distearate, Cocomide MIPA, Sodium Benzoate, Polyquaternium 7, Disodium EDTA, Lime Oil, Phenoxyethanol, Citric Acid, Tocopheryl Acetate, Panthenol.

Packaging

INSTANT EFFECT-PLUS FORMULA

Clean,Sanitize and Moisture

Free of paraben, dye and phthalates

ANTIBACTERIAL LIQUID SOAP

- Sanitizing formula to help reduce cross-contamination

- Hands feel smooth, soft and refreshed

Distributed by

PBITTS LLC

836 Foster Ave Bensenville

ILLINOIS 60106

Manufacturing Company

Asilnur Gıda ve Kimya San. Tic. Ltd. Şti.

formulated by: Aziz Aydın

MADE IN TURKEY

Packaging